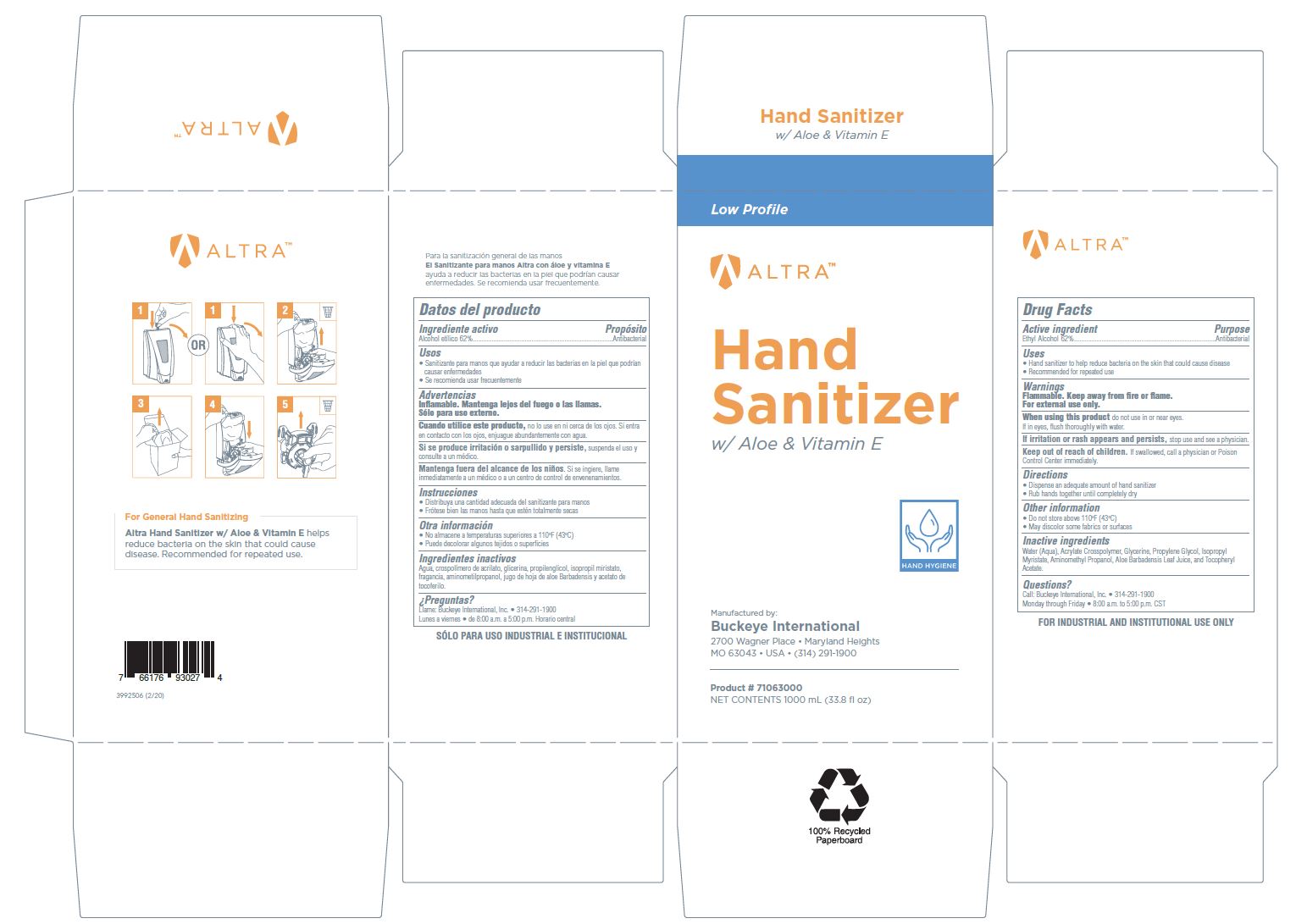 DRUG LABEL: Altra Hand Sanitizer with Aloe and Vitamin E
NDC: 30805-014 | Form: SOLUTION
Manufacturer: Buckeye International, Inc.
Category: otc | Type: HUMAN OTC DRUG LABEL
Date: 20240723

ACTIVE INGREDIENTS: ALCOHOL 62 mL/100 mL
INACTIVE INGREDIENTS: ISOPROPYL MYRISTATE; ALOE VERA LEAF; .ALPHA.-TOCOPHEROL ACETATE; PROPYLENE GLYCOL; AMINOMETHYLPROPANOL; WATER; GLYCERIN; CARBOMER INTERPOLYMER TYPE A (ALLYL SUCROSE CROSSLINKED)

Drug Facts 30805-014

Active ingredient

Ethyl Alcohol 62%

Purpose

Antibacterial

Uses

- Hand sanitizer to help reduce bacteria on the skin that could cause disease
- Recommended for repeated use

Warnings

Flammable. Keep away from fire or flame.

For external use only.

WHEN USING

When using this productdo not use in or near eyes.

If in eyes, flush thoroughly with water.

STOP USE

If irritation or rash appears and persists, stop use and see a physician.

Keep out of reach of children.If swallowed, call a physician or Poison Control Center immediately.

Directions

- Dispense an adequate amount of hand sanitizer
- Rub hands togetheruntil completely dry

Other information

- Do not store above 110 F (43 C)
- May discolor some fabrics or surfaces

Inactive ingredients

Water (Aqua), Acrylate Crosspolymer, Glycerine, Propylene Glycol, Isopropyl Myristate, Aminomethyl Propanol, Aloe Barbadensis Leaf Juice, and Tocopheryl Acetate.

Questions?

Call Buckeye International, Inc. 314-291-1900

Monday through Friday 8:00 a.m. to 5:00 p.m. CST

PACKAGE LABEL

Low Profile

Altra

Hand Sanitizer

with Aloe and Vitamin E

Manufactured by:

Buckeye International

2700 Wagner Place Maryland Heights

MO 63043 USA (314) 291-1900

Product # 71063000

Net Contents 1000 mL (33.8 fl oz)